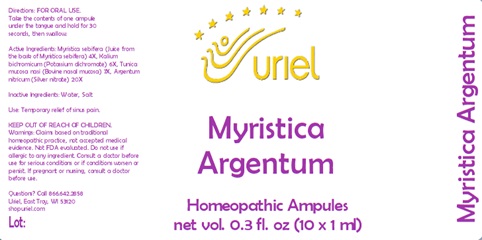 DRUG LABEL: Myristica Argentum
NDC: 48951-7062 | Form: LIQUID
Manufacturer: Uriel Pharmacy Inc.
Category: homeopathic | Type: HUMAN OTC DRUG LABEL
Date: 20240308

ACTIVE INGREDIENTS: BOS TAURUS NASAL MUCOSA 7 [hp_X]/1 mL; SILVER 20 [hp_X]/1 mL; VIROLA SEBIFERA RESIN 4 [hp_X]/1 mL; DICHROMATE ION 6 [hp_X]/1 mL
INACTIVE INGREDIENTS: WATER; SODIUM CHLORIDE

Myristica Argentum

INDICATIONS AND USAGE

Directions: FOR ORAL USE.

DOSAGE AND ADMINISTRATION

Take the contents of one ampule under the tongue and hold for 30 seconds, then swallow.

ACTIVE INGREDIENT

Active Ingredients: Myristica sebifera (Juice from the bark of Myristica sebifera) 4X, Kalium bichromicum (Potassium dichromate) 6X, Tunica mucosa nasi (Bovine nasal mucosa) 7X, Argentum nitricum (Silver nitrate) 20X

Inactive Ingredients: Water, Salt

PURPOSE

Use: Temporary relief of sinus pain.

KEEP OUT OF REACH OF CHILDREN.

WARNINGS

Warnings: Claims based on traditional homeopathic practice, not accepted medical evidence. Not FDA evaluated. Do not use if allergic to any ingredient. Consult a doctor before use for serious conditions or if conditions worsen or persist. If pregnant or nursing, consult a doctor before use.

Questions? Call 866.642.2858
Uriel, East Troy, WI 53120
www.urielpharmacy.com